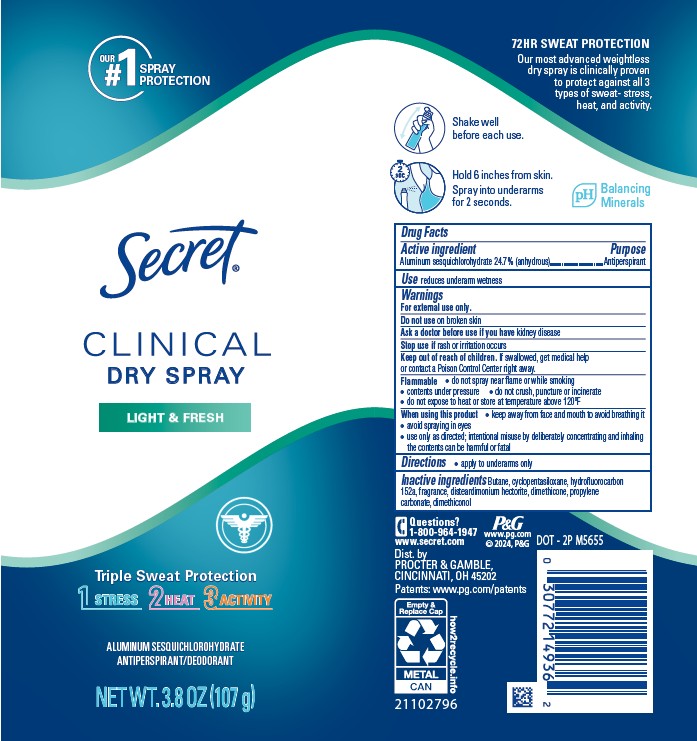 DRUG LABEL: Secret Clinical Dry Light and Fresh
NDC: 84126-185 | Form: AEROSOL, SPRAY
Manufacturer: The Procter & Gamble Manufacturing Company
Category: otc | Type: HUMAN OTC DRUG LABEL
Date: 20251029

ACTIVE INGREDIENTS: ALUMINUM SESQUICHLOROHYDRATE 24.7 g/100 g
INACTIVE INGREDIENTS: BUTANE; DISTEARDIMONIUM HECTORITE; DIMETHICONE; DIMETHICONOL (100000 CST); PROPYLENE CARBONATE; CYCLOPENTASILOXANE; HYDROFLUOROCARBON 152A

Secret Clinical Dry Spray Light and Fresh

Drug Facts

Active ingredient

Aluminum sesquichlorohydrate 24.7.0% (anhydrous)

Purpose

Antiperspirant

Use

- reduces underarm wetness

Warnings

For external use only.

Do not use on broken skin

Ask a doctor before use if you have kidney disease

Stop use if rash or irritation occurs

Keep out of reach of children. If swallowed, get medical help or contact a Poison Control Center right away.

Flammable

do not spray near flame or while smoking

contents under pressure
do not crush, puncture or incinerate

do not expose to heat or store at temperature above 120ºF

When using this product

keep away from face and mouth to avoid breathing it

avoid spraying in eyes

use only as directed; intentional misuse by deliberately concentrating and inhaling the contents can be harmful or fatal

Directions

- apply to underarms only

Inactive ingredients

Butane, cyclopentasiloxane, hydrofluorocarbon 152A, fragrance, disteardimonium hectorite, dimethicone, propylene carbonate, dimethiconol

Dist. by PROCTER & GAMBLE,
CINCINNATI, OH 45202.

Questions or comments?

1-800-964-1947

PRINCIPAL DISPLAY PANEL - 107 g Can

Secret ®

CLINICAL

DRY SPRAY

LIGHT & FRESH

ALUMINUM SESQUICHLOROHYDRATE

ANTIPERSPIRANT/DEODORANT

NET WT. 3.8 OZ (107 g)